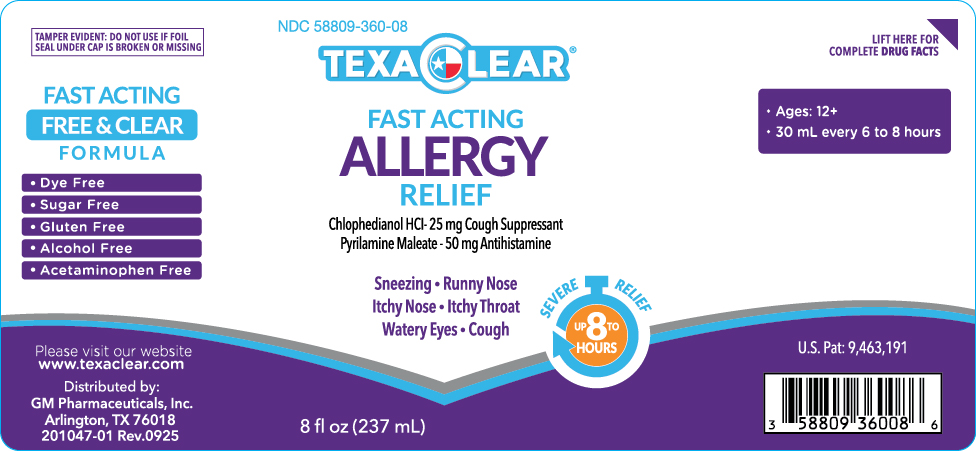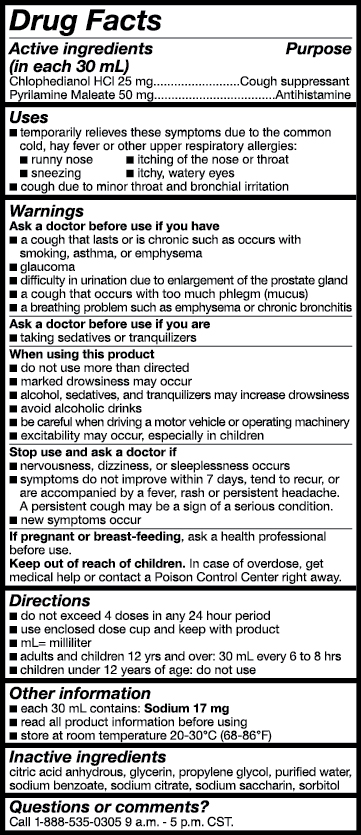 DRUG LABEL: Texaclear Fast Acting Allergy Relief
NDC: 58809-360 | Form: LIQUID
Manufacturer: GM Pharmaceuticals, INC
Category: otc | Type: HUMAN OTC DRUG LABEL
Date: 20251103

ACTIVE INGREDIENTS: CHLOPHEDIANOL HYDROCHLORIDE 25 mg/30 mL; PYRILAMINE MALEATE 50 mg/30 mL
INACTIVE INGREDIENTS: ANHYDROUS CITRIC ACID; GLYCERIN; PROPYLENE GLYCOL; WATER; SODIUM CITRATE; SACCHARIN SODIUM; SORBITOL

TexaClear Fast Acting Allergy Relief

(Chlophedianol HCI & Pyrilamine Maleate), solution

GM Pharmaceuticals, Inc.

Drug Facts

Active ingredients (in each 30 mL)

Chlophedianol HCl 25 mg

Pyrilamine Maleate 50 mg

Purpose

Cough suppressant

Antihistamine

Uses

■ temporarily relieves these symptoms due to the common cold, hay fever or other upper respiratory allergies:

■ runny nose

■ sneezing

■ itching of the nose or throat

■ itchy, watery eyes

■ cough due to minor throat and bronchial irritation

Warnings

Ask a doctor before use if you have

■ a cough that lasts or is chronic such as occurs with smoking, asthma, or emphysema

■ glaucoma

■ difficulty in urination due to enlargement of the prostate gland

■ a cough that occurs with too much phlegm (mucus)

■ a breathing problem such as emphysema or chronic bronchitis

Ask a doctor before use if you are

■ taking sedative or tranquilizers

When using this product

■ do not use more than directed

■ marked drowsiness may occur

■ alcohol, sedatives, and tranquilizers may increase drowsiness

■ avoid alcoholic drinks

■ be careful when driving a motor vehicle or operating machinery

■ excitability may occur, especially in children

Stop use and ask a doctor if

■ nervousness, dizziness, or sleeplessness occurs

■ symptoms do not improve within 7 days, tend to recur, or are accompanied by a fever, rash or persistent headache. A persistent cough may be a sign of a serious condition.

■ new symptoms occur

If pregnant or breast-feeding,

ask a health professional before use.

Keep out of reach of children.

In case of overdose, get medical help or contact a Poison Control Center right away.

Directions

■ do not exceed 4 doses in any 24 hour period

■ use enclosed dose cup and keep with product

■ mL= milliliter

■ adults and children 12 yrs and over: 30 mL every 6 to 8 hrs

■ children under 12 years of age: do not use

Other information

■ each 30 mL contains: Sodium 17 mg

■ read all product information before using

■ store at room temperature 20-30°C (68-86°F)

Inactive ingredients

citric acid anhydrous, glycerin, propylene glycol, purified water, sodium benzoate, sodium citrate, sodium saccharin, sorbitol

Questions or comments?

Call 1-888-535-0305 9 a.m. - 5 p.m. CST.

PRINCIPAL DISPLAY PANEL

NDC 58809-360-08
TEXACLEAR
FAST ACTING
ALLERGY
RELIEF
8 fl oz (237 mL)